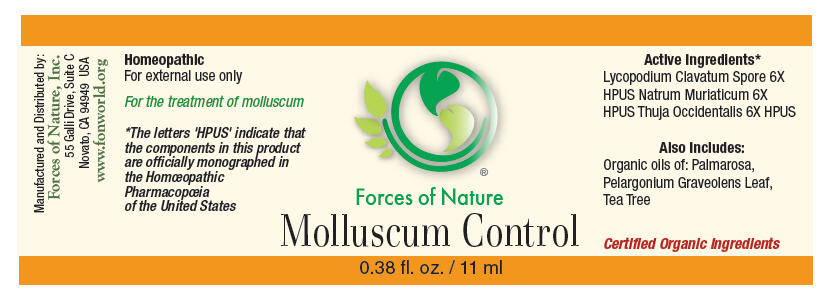 DRUG LABEL: Molluscum Control
NDC: 51393-6777 | Form: SOLUTION/ DROPS
Manufacturer: Forces of Nature
Category: homeopathic | Type: HUMAN OTC DRUG LABEL
Date: 20100824

ACTIVE INGREDIENTS: Lycopodium clavatum Spore 6 [hp_X]/1000 mL; SODIUM CHLORIDE 6 [hp_X]/1000 mL; Thuja occidentalis leafy twig 6 [hp_X]/1000 mL

Molluscum Control

Drug Facts

Indications

For the treatment of moles.

ACTIVE INGREDIENT

PURPOSE

Homeopathic Active Ingredients [The letters 'HPUS' indicate that the components in this product are officially monographed in the Homœopathic Pharmacopœia of the United States.]
Equal parts of: | Purpose
Lycopodium Clavatum Spore 6X HPUS | Remedy for Molluscum, skin eruptions
Natrum Muriaticum 6X HPUS | Relief for Molluscum, skin conditions and inflammation
Thuja occidentalis 6X HPUS | Remedy for skin irritations that itch or burn

Inactive Ingredients

Palmarosa Oil, Pelargonium Graveolens Leaf Oil, Tea Tree Oil

Directions

Apply directly to infected area. Product is very concentrated, apply only enough to cover area and gently rub into the skin. For more sensitive skin, apply product to a cotton swab and dab to area. Apply 3 times per day. For external use only. Avoid contact to eyes. Discontinue use if continued skin irritation occurs.

Warnings

WHEN USING

This product does not prevent the spread of molluscum. If skin symptoms worsen, redness, bleeding or pus occurs consult a health care professional. Some individuals may be sensitive to tea tree or other oils. Begin with a small drop to determine if the product causes any increased redness or irritation and discontinue use if it irritates your skin.

PREGNANCY OR BREAST FEEDING

If you are pregnant or breast-feeding, ask a health professional before use.

KEEP OUT OF REACH OF CHILDREN

Keep out of the reach of children. If accidental ingestion, get medical help or contact a Poison Control Center.

STOP USE

For external use only. Do not apply to the eyes or mucous membranes. Keep all medicines out of the reach of children. Stop use and ask a doctor if condition worsens.

Manufactured by:
Forces of Nature, Inc.
55 Galli Drive, Suite C
Novato, CA 94949 USA
www.fonworld.org

Product questions?

877-975-3797

NDC #: 51393-6777-1 (11ml) // 51393-6777-2 (33ml)

PRINCIPAL DISPLAY PANEL - 11 ml Bottle Label

Forces of Nature

Molluscum Control

0.38 fl. oz. / 11 ml